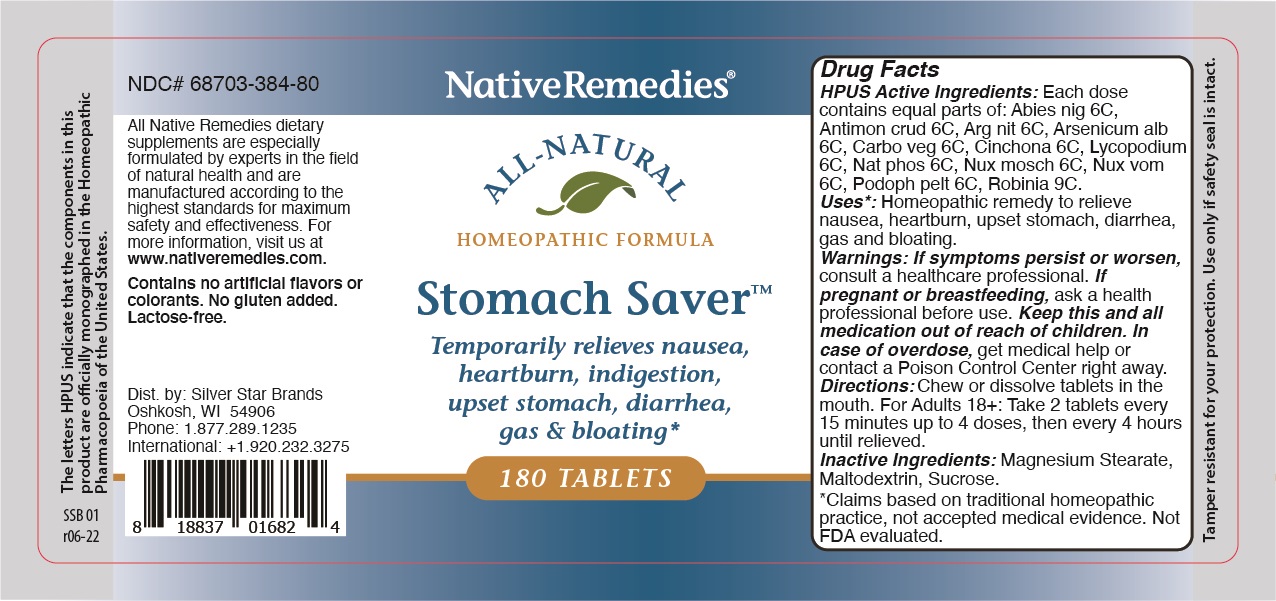 DRUG LABEL: Stomach Saver
NDC: 68703-384 | Form: TABLET
Manufacturer: Silver Star Brands
Category: homeopathic | Type: HUMAN OTC DRUG LABEL
Date: 20220527

ACTIVE INGREDIENTS: SODIUM PHOSPHATE, DIBASIC 6 [hp_C]/1 1; STRYCHNOS NUX-VOMICA SEED 6 [hp_C]/1 1; SILVER NITRATE 6 [hp_C]/1 1; ROBINIA PSEUDOACACIA BARK 6 [hp_C]/1 1; NUTMEG 6 [hp_C]/1 1; ARSENIC TRIOXIDE 6 [hp_C]/1 1; ACTIVATED CHARCOAL 6 [hp_C]/1 1; PODOPHYLLUM PELTATUM ROOT 6 [hp_C]/1 1; LYCOPODIUM CLAVATUM SPORE 6 [hp_C]/1 1; ANTIMONY TRISULFIDE 6 [hp_C]/1 1; CINCHONA OFFICINALIS BARK 6 [hp_C]/1 1; PICEA MARIANA RESIN 6 [hp_C]/1 1
INACTIVE INGREDIENTS: SUCROSE; MAGNESIUM STEARATE; MALTODEXTRIN

NativeRemedies® Stomach Saver™

HPUS Active Ingredients: Each dose contains equal parts of: Abies nig 6C, Antimon crud 6C, Arg nit 6C, Arsenicum alb 6C, Carbo veg 6C, Cinchona 6C, Lycopodium 6C, Nat phos 6C, Nux mosch 6C, Nux vom 6C, Podoph pell 6C, Robinia 9C.

*Claims based on traditional homeopathic practice, not accepted medical evidence. Not FDA evaluated.

The letters HPUS indicate that the components in this product are officially monographed in the Homeopathic Pharmacopoeia of the United States.

Uses*

Uses*: Homeopathic remedy to relieve nausea, heartburn, upset stomach, diarrhea, gas and bloating.

*Claims based on traditional homeopathic practice, not accepted medical evidence. Not FDA evaluated.

Directions

Directions: Chew or dissolve tablets in the mouth. For Adults 18+: Take 2 tablets every 15 minutes up to 4 doses, then every 4 hours until relieved.

OTHER SAFETY INFORMATION

Contains no artificial flavors or colorants. No gluten added. Lactose-free.

Inactive ingredients

Inactive ingredients: Magnesium Stearate, Maltodextrin, Sucrose.

KEEP OUT OF REACH OF CHILDREN

Keep this and all medication out of reach of children. In case of overdose, get medical help or contact a Poison Control center right away.

PREGNANCY OR BREAST FEEDING

If pregnant or breastfeeding, ask a health professional before use.

PURPOSE

Temporarily relieves nausea, heartburn, indigestion, upset stomach, diarrhea, gas & bloating.

Directions

Directions: Chew or dissolve tablets in the mouth. For Adults 18+: Take 2 tablets every 15 minutes up to 4 doses, then every 4 hours until relieved.